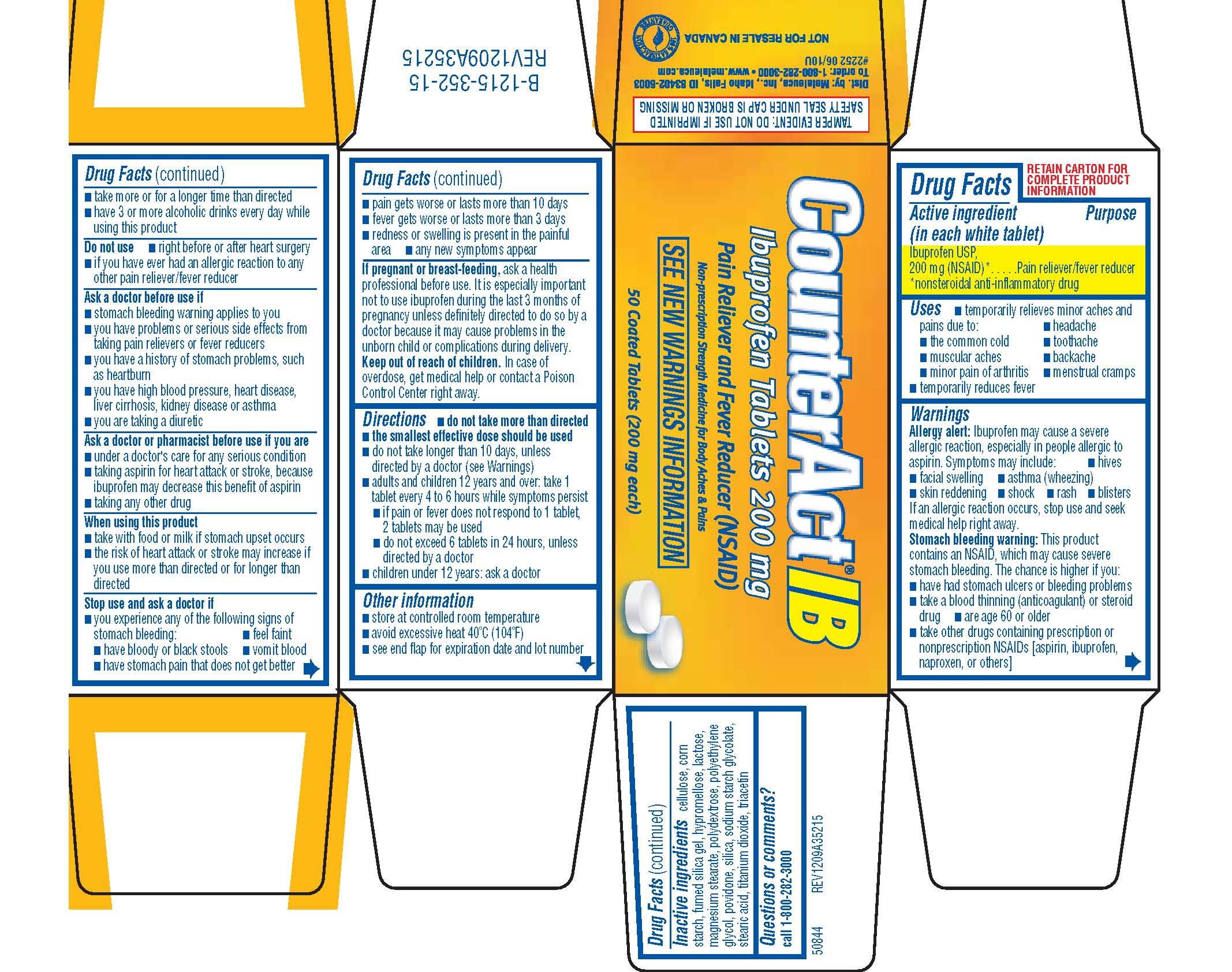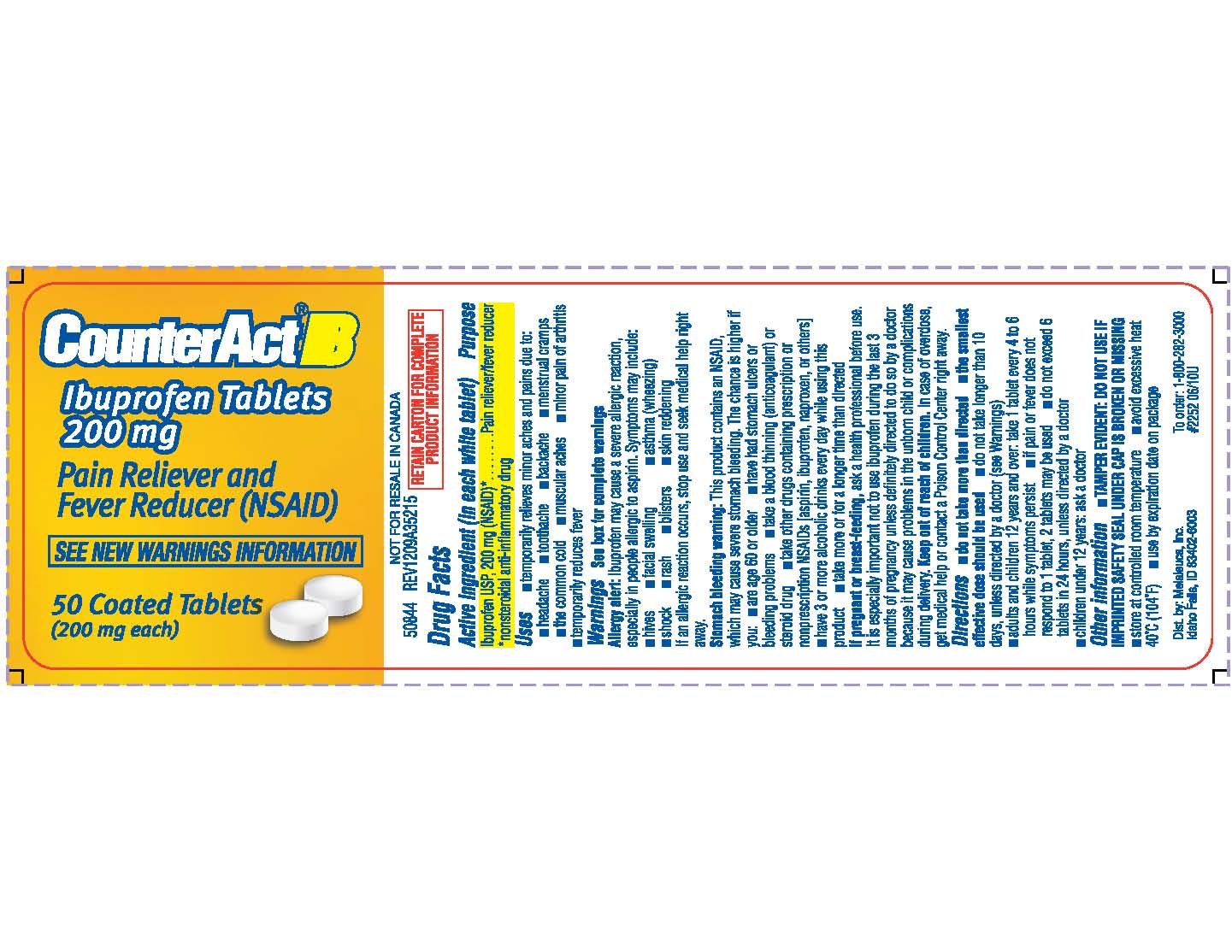 DRUG LABEL: CounterAct
NDC: 54473-134 | Form: TABLET, FILM COATED
Manufacturer: Melaleuca, Inc.
Category: otc | Type: HUMAN OTC DRUG LABEL
Date: 20110419

ACTIVE INGREDIENTS: IBUPROFEN 200 mg/1 1
INACTIVE INGREDIENTS: CELLULOSE, MICROCRYSTALLINE; HYPROMELLOSES; LACTOSE; MAGNESIUM STEARATE; POLYDEXTROSE; POLYETHYLENE GLYCOL; POVIDONE; SILICON DIOXIDE; SODIUM STARCH GLYCOLATE TYPE A POTATO; STARCH, CORN; STEARIC ACID; TITANIUM DIOXIDE; TRIACETIN

CounterAct IB Content of Label

Active ingredient (in each white tablet)
Ibuprofen USP, 200 mg (NSAID)*
*nonsteroidal anti-inflammatory drug

Purpose
Pain reliever/fever reducer

Use

- temporarily relieves minor aches and pains due to:
-
  - headache
  - the common cold
  - toothache
  - muscular aches
  - backache
  - minor pain of arthritis
  - menstrual cramps
- temporarily relieves fever

Warnings
Allergy alert: Ibuprofen may cause severe allergic reaction, especially in people allergic to aspirin. Symptoms may include:

- hives
- facial swelling
- asthma (wheezing)
- skin reddening
- shock
- rash
- blisters

If an allergic reaction occurs, stop use and seek medical help right away.
Stomach bleeding warning: This product contains an NSAID, which may cause severe stomach bleeding. The chance is higher if you:

- have had stomach ulcers or bleeding problems
- take a blood thinning (anticoagulant) or steroid drug
- are age 60 or older
- take other drugs containing prescription or nonprescription NSAIDs [aspirin, ibuprofen, naproxen, or others]
- take more or for a longer time than directed
- have 3 or more alcoholic drinks every day while using this product

Do not use

- right before or after heart surgery
- if you have ever had an allergic reaction to any other pain reliever/fever reducer

Ask a doctor before use if

- stomach bleeding warning applies to you
- you have problems or serious side effects from taking pain relievers or fever reducers
- you have a history of stomach problems, such as heartburn
- you have high blood pressure, heart disease, liver cirrhosis, kidney disease or asthma
- you are taking a diuretic

Ask a doctor or pharmacist before use if you are

- under a doctor's care for any serious condition
- taking aspirin for heart attack or stroke, because ibuprofen may decrease this benefit of aspirin
- taking any other drug

When using this product

- take with food or milk if stomach upset occurs
- the risk of heart attack or stroke may increase if you use more than directed or for longer than directed

Stop use and ask a doctor if

- you experience any of the following signs of stomach bleeding:
-
  - feel faint
  - have bloody or black stools
  - vomit blood
  - have stomach pain that does not get better
- pain gets worse or lasts more than 10 days
- fever gets worse or lasts more than 3 days
- redness or swelling is present in the painful area
- any new symptoms appear

PREGNANCY OR BREAST FEEDING

If pregnant or breast-feeding, ask a health professional before use. It is especially important not to use ibuprofen during the last 3 months of pregnancy unless definitely directed to do so by a doctor because it may cause problems in the unborn child or complications during delivery.

Keep out of reach of children. In case of overdose, get medical help or contact a Poison Control Center right away.

Directions

- do not take more than directed
- the smallest effective dose should be used

- do not take longer than 10 days, unless directed by a doctor (see Warnings)
- adults and children 12 years and over: take 1 tablet every 4 to 6 hours while symptoms persist
-
  - if pain or fever does not respond to 1 tablet, 2 tablets may be used
  - do not exceed 6 tablets in 24 hours, unless directed by a doctor
- children under 12 years: ask a doctor

Other information

- store at controlled room temperature
- avoid excessive heat 40°C (104°F)

INACTIVE INGREDIENT

Inactive ingredients cellulose, corn starch, fumed silica gel, hypromellose, lactose, magnesium stearate, polydextrose, polyethylene glycol, povidone, silica, sodium starch glycolate, stearic acid, titanium dioxide, triacetin

Questions or comments?
call 1-800-282-3000

BOXED WARNING

TAMPER EVIDENT: DO NOT USE IF IMPRINTED SAFETY SEAL UNDER CAP IS BROKEN OR MISSING